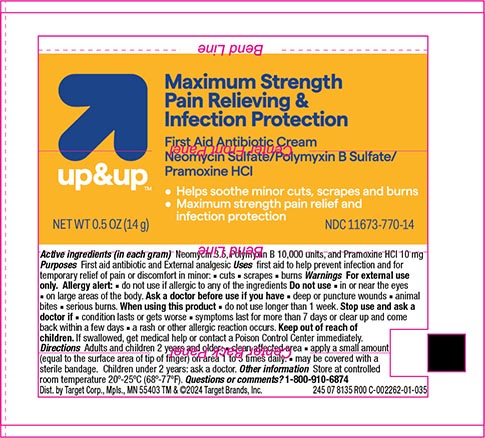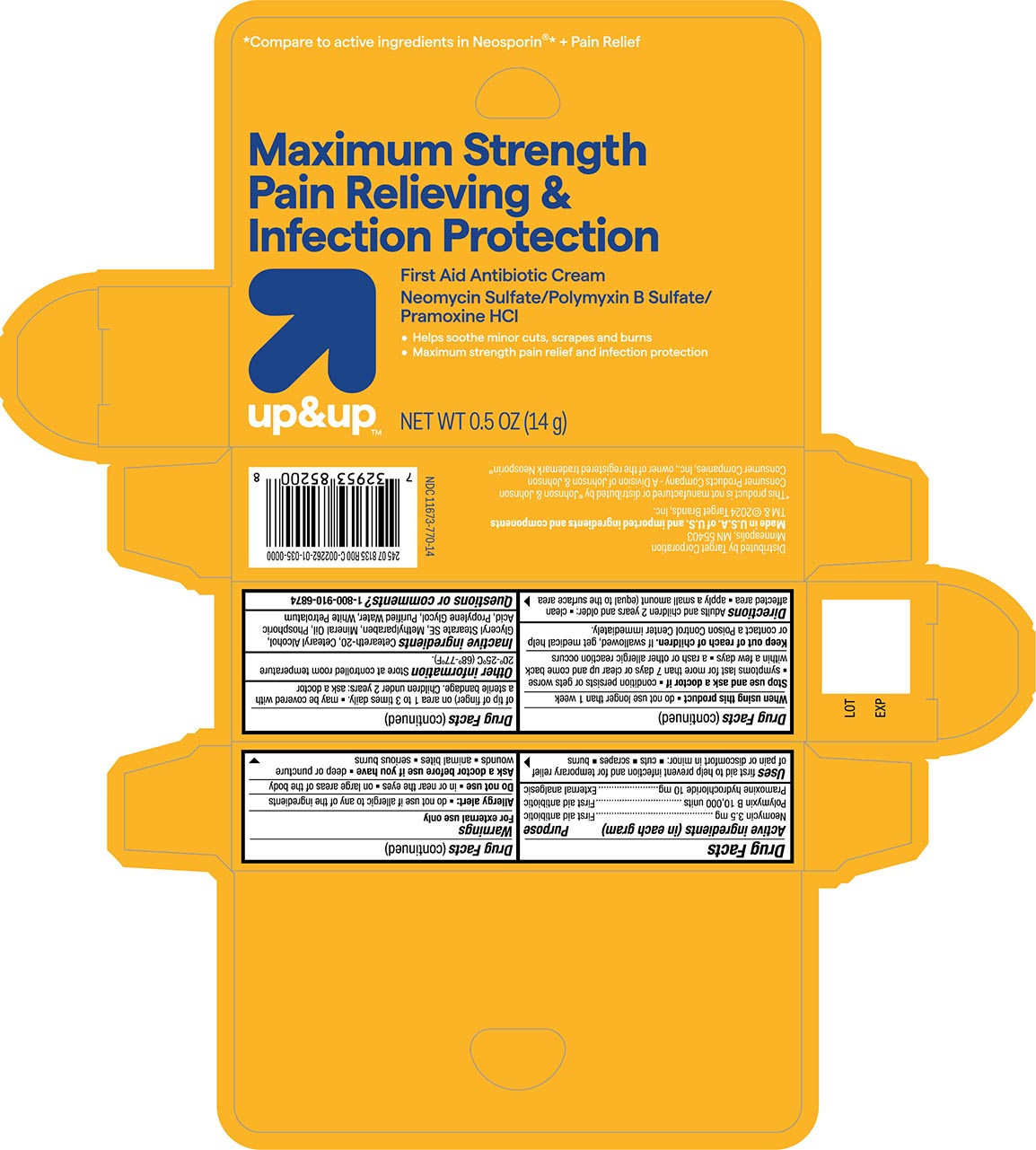 DRUG LABEL: Antibiotic and Pain Relief
NDC: 11673-770 | Form: CREAM
Manufacturer: Target Corporation
Category: otc | Type: HUMAN OTC DRUG LABEL
Date: 20240118

ACTIVE INGREDIENTS: POLYMYXIN B SULFATE 10000 [USP'U]/1 g; NEOMYCIN SULFATE 3.5 mg/1 g; PRAMOXINE HYDROCHLORIDE 10 mg/1 g
INACTIVE INGREDIENTS: POLYOXYL 20 CETOSTEARYL ETHER; CETOSTEARYL ALCOHOL; GLYCERYL STEARATE SE; METHYLPARABEN; MINERAL OIL; PHOSPHORIC ACID; PROPYLENE GLYCOL; WATER; PETROLATUM

Target Up &Up Antibiotic+Pain Relief Cream

Active ingredients

Neomycin Sulfate (3.5mg)
Polymixin B Sulfate (10,000 units)
Pramoxine Hydrochloride (10 mg)

Purpose

First Aid Antibiotic
First Aid Antibiotic
External Analgesic

Uses

first aid to prevent infection and for the temporary relief of pain or discomfort in minor:

- cuts
- scapes
- burns

Warnings For external use only

Allergy alert

- do not use if you are allergic to any of the ingredients

Do not use

- in or near the eyes
- or on large areas of the body

Ask a doctor before use if you have

- deep or puncture wounds
- animal bites
- serious burns

Stop use and ask a doctor if

- condition persists or gets worse
- symptoms last for more than 7 days or clear up and come back within a few days
- a rash or other allergic reaction develops

KEEP OUT OF REACH OF CHILDREN

Keep out of the reach of children. If swallowed get medical help or contact a Poison Control Center immediately.

Directions

- clean the affected area
- apply a small amount (equal to surface area of tip of finger) on the area 1 to 3 times daily.
- may be covered with a sterile bandage

Other inofrmation

Store at a controlled room temperature 68º-77ºF (20º-25ºC)

Inactive ingredients

Ceteareth-20, Cetearyl Alcohol, Glyceryl Stearate SE, Methylparaben, Mineral Oil, Phosphoric Acid, Propylene Glycol, Purified Water, White Petrolatum

Principal Display Panel

Target up&Up NDC 11673-770-14

Maximum Strength Pain Releiving & Infection Protection

Neomycin Sulfate/ Polymyxin B Sulfate / Pramoxine HCL

NET WT 0.5oz (14g)